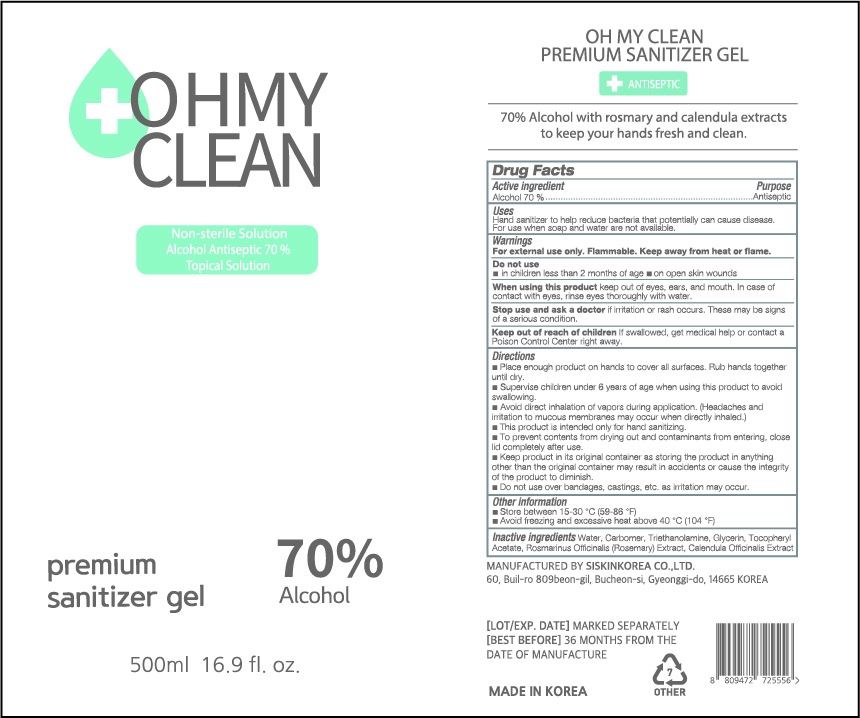 DRUG LABEL: OH MY CLEAN PREMIUM SANITIZER Gel
NDC: 74514-0570 | Form: GEL
Manufacturer: SISKINKOREA CO.,LTD.
Category: otc | Type: HUMAN OTC DRUG LABEL
Date: 20200423

ACTIVE INGREDIENTS: ALCOHOL 350 mL/500 mL
INACTIVE INGREDIENTS: TROLAMINE; GLYCERIN; .ALPHA.-TOCOPHEROL ACETATE; CALENDULA OFFICINALIS WHOLE; WATER; ROSEMARY; CARBOMER HOMOPOLYMER, UNSPECIFIED TYPE

[08 R] 500ml_70%_gel_OH MY CLEAN PREMIUM SANITIZER GEL [74514-0570-1]